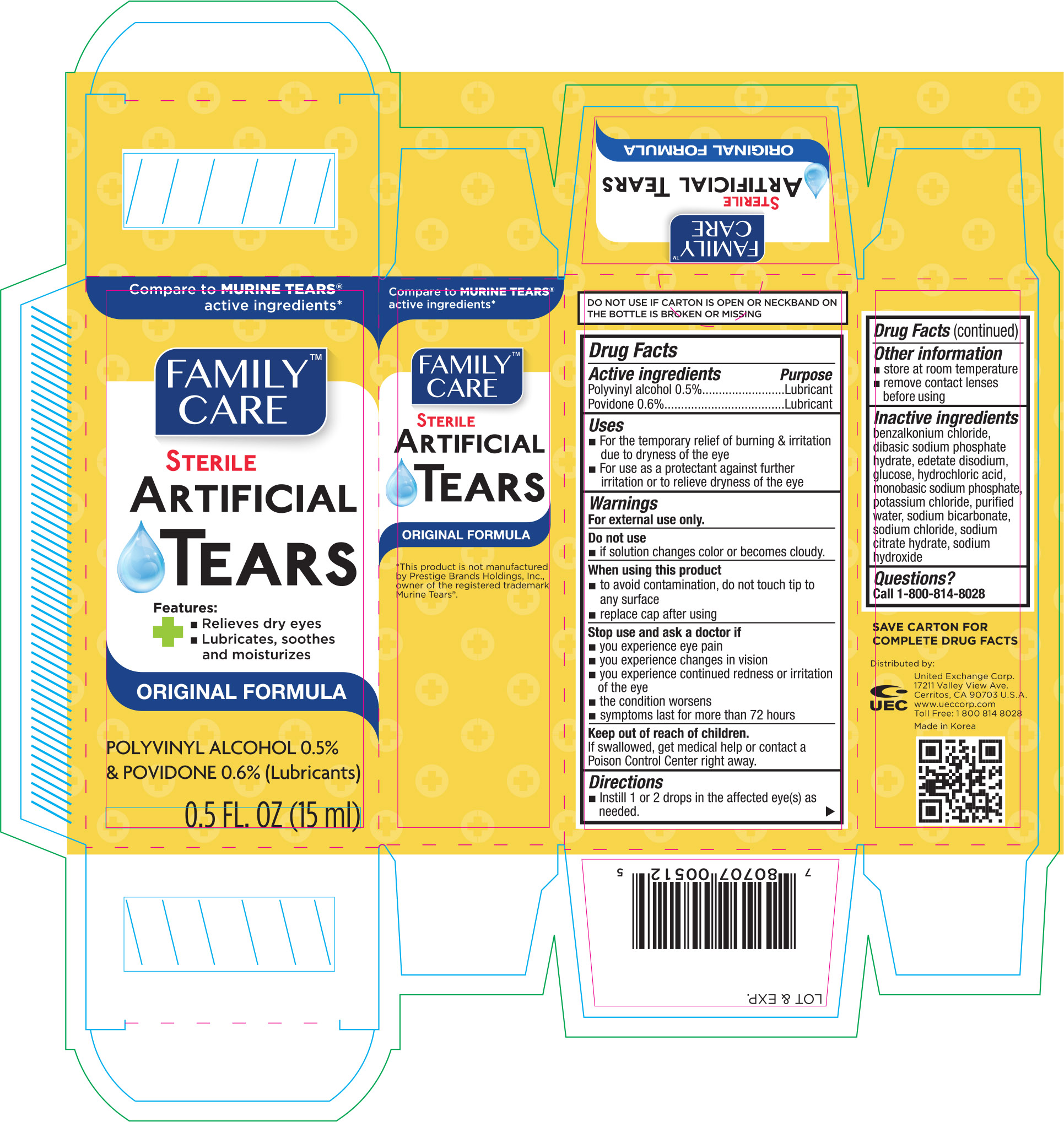 DRUG LABEL: Family Care Artificial Eye
NDC: 65923-512 | Form: SOLUTION/ DROPS
Manufacturer: United Exchange Corp.
Category: otc | Type: HUMAN OTC DRUG LABEL
Date: 20160422

ACTIVE INGREDIENTS: POLYVINYL ALCOHOL, UNSPECIFIED .05 mg/1 mL; POVIDONES .06 mg/1 mL
INACTIVE INGREDIENTS: BENZALKONIUM CHLORIDE; SODIUM PHOSPHATE, DIBASIC DIHYDRATE; EDETATE DISODIUM; HYDROCHLORIC ACID; SODIUM PHOSPHATE, MONOBASIC; POTASSIUM CHLORIDE; WATER; SODIUM BICARBONATE; SODIUM CHLORIDE; SODIUM CITRATE; SODIUM HYDROXIDE

Active ingredients Purpose

Polyvinyl alcohol 0.5%....................................Lubricant

Povidone 0.6%..............................................Lubricant

Uses

- For the temporary relief of burning & irritation due to dryness of the eye
- For use as a protectant against further irritation or to relieve dryness of the eye

Warnings

For external use only.

Do not use

- if solution changes color or becomes cloudy.

When using this product

- to avoid contamination, do not touch tip to any surface
- replace cap after using

Stop use and ask a doctor if

- you experience eye pain
- you experience changes in vision
- you experience continued redness or irritation of the eye
- the condition worsens
- symptoms last for more than 72 hours

Keep out of reach of children.

If swallowed, get medical help or contact a Poison Control Center right away.

Directions

- Instill 1 or 2 drops in the affected eye(s) as needed.

Other information

- store at room temperature
- remove contact lenses before using

Inactive ingredients

benzalkonium chloride, dibasic sodium phosphate hydrate, edetate disodium, glucose, hydrochloric acid, monobasic sodium phosphate, potassium chloride, purified water, sodium bicarbonate, sodium chloride, sodium citrate hydrate, sodium hydroxide

DOSAGE AND ADMINISTRATION

Distributed by:

United Exchange Corp.

17211 Valley View Ave.

Cerritos, CA 90703 U.S.A.

www.ueccorp.com

Toll Free: 1 800 814 8028

Made in Korea